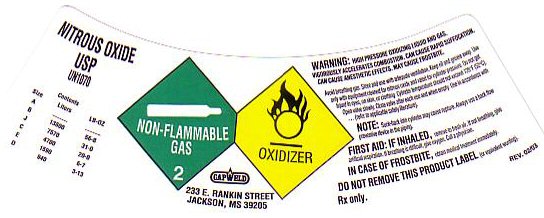 DRUG LABEL: NITROUS OXIDE
NDC: 52849-500 | Form: GAS
Manufacturer: Capweld Inc
Category: prescription | Type: HUMAN PRESCRIPTION DRUG LABEL
Date: 20100101

ACTIVE INGREDIENTS: NITROUS OXIDE 99 L/100 L

NITROUS OXIDE COMPRESSED LABEL

USP NITROUS OXIDE, COMPRESSED UN 1070
WARNING: HIGH PRESSURE OXIDIZING LIQUID AND GAS VIGOROUSLY ACCELERATES COMBUSTION CAN CAUSE RAPID SUFFOCATION CAN CAUSE ANESTHETIC EFFECTS MAY CAUSE FROSTBITE Avoid breathing gas. Store and use with adequate ventilation Keep oil and grease away Use only with equipment cleaned for nitrous oxide service and rated for cylinder pressure Do not get liquid in eyes, on skin, or clothing. Cylinder temperature should not exceed 52 C (125 F) Open valve slowly Close valve when not in use and when empty. Use in accordance with (refer to acceptable safety literature).

Note: Suck back into cylinder may cause rupture. Always use a back flow preventive device in the piping.
FIRST AID: If inhaled, remove to fresh air. If not breathing, give
artificial respiration. If breathing is difficult, give oxygen. Call
a physician.
Do Not Remove this Product Label

GENERAL WARNINGS AND PRECAUTIONS

Rx Only